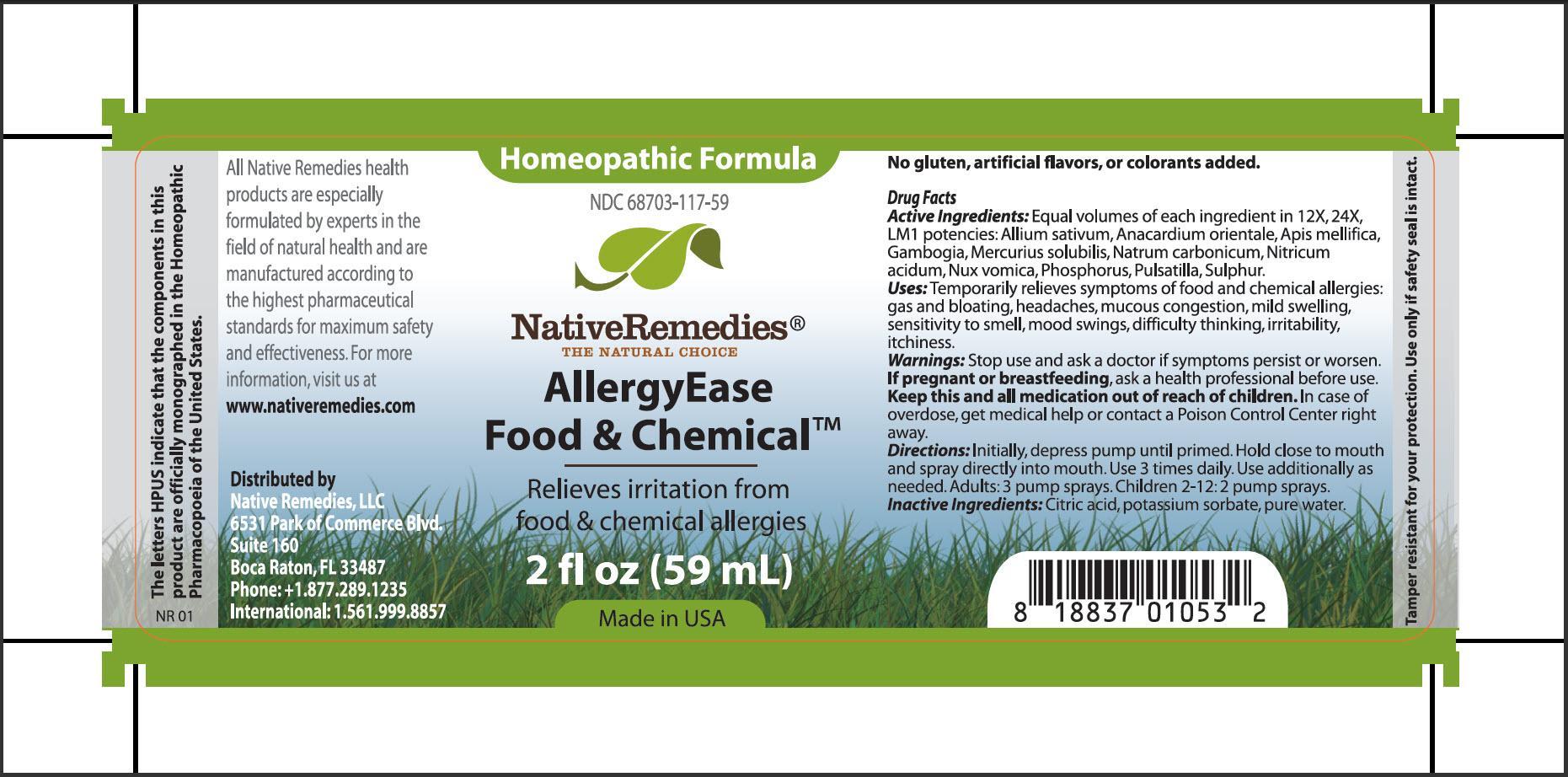 DRUG LABEL: AllerguEase Food and Chemical
NDC: 68703-117 | Form: SPRAY
Manufacturer: Native Remedies, LLC
Category: homeopathic | Type: HUMAN OTC DRUG LABEL
Date: 20130702

ACTIVE INGREDIENTS: GARLIC 12 [hp_X]/59 mL; SEMECARPUS ANACARDIUM JUICE 12 [hp_X]/59 mL; APIS MELLIFERA 12 [hp_X]/59 mL; GAMBOGE  12 [hp_X]/59 mL; MERCURIUS SOLUBILIS 12 [hp_X]/59 mL; SODIUM CARBONATE 12 [hp_X]/59 mL; NITRIC ACID 12 [hp_X]/59 mL; STRYCHNOS NUX-VOMICA SEED 12 [hp_X]/59 mL; PHOSPHORUS 12 [hp_X]/59 mL; PULSATILLA VULGARIS 12 [hp_X]/59 mL; SULFUR 12 [hp_X]/59 mL
INACTIVE INGREDIENTS: CITRIC ACID MONOHYDRATE; POTASSIUM SORBATE; WATER

AllergyEase Food and Chemical

PURPOSE

Relieves irritation from food and chemical allergies

Drug Facts
Active Ingredients: Equal volumes of each ingredient in 12X, 24X, LM1 potencies: Allium sativum, Anacardium orientale, Apis mellifica, Gambogia, Mercuris solubilis, Natrum carbonicum, Nitricum acidum, Nux vomica, Phosphorus, Pulsatilla, Sulphur

INDICATIONS AND USAGE

Uses:Temporary relieves symptoms of food and chemical allergies: gas and bloating, headaches, mucous congestion, mild swelling, sensitivity to smell, mood swings, difficulty thinking, irritability, itchiness

WARNINGS

Warnings:Stop use and ask a doctor if symptoms persist or worsen

PREGNANCY OR BREAST FEEDING

If pregnant or breastfeeding, ask a health professional before use

KEEP OUT OF REACH OF CHILDREN

Keep this and all medication out of reach of children

OVERDOSAGE

In case of overdose, get medical help or contact a Poison Control Center right away

DOSAGE AND ADMINISTRATION

Directions: Initially, depress pump until primed. Hold close to mouth and spray directly into mouth. Use 3 times daily. Use additionally as needed. Adults: 3 pump sprays. Children 2-12: 2 pump sprays

Inactive Ingredients: Citric acid, potassium sorbate, pure water

PATIENT COUNSELING INFORMATION

The letters HPUS, indicate that the components in this product are officially monographed in the Homeopathic Pharmacopoeia of the Unites States

All Native Remedies health products are especially formulated by experts in the field of natural health and are manufactured according to the highest pharmaceutical standards for maximum safety and effectiveness. For more information, visit us at www.nativeremedies.com

Distributed by
Native Remedies, LLC
6531 Park of Commerce Blvd.
Suite 160
Boca Raton, FL 33487
Phone: 1.877.289.1235
International: 1.561.999.8857

No gluten, artificial flavors, or colorants added

STORAGE AND HANDLING

Tamper resistant for you protection. Use only if safety seal is intact